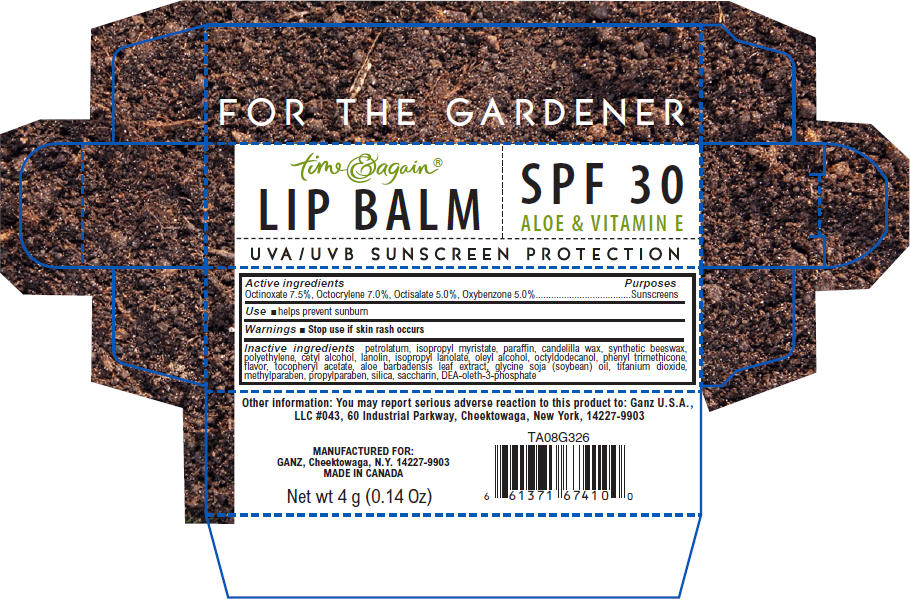 DRUG LABEL: FOR THE GARDENER LIP BALM 
NDC: 75862-018 | Form: STICK
Manufacturer: GANZ U.S.A., LLC
Category: otc | Type: HUMAN OTC DRUG LABEL
Date: 20110816

ACTIVE INGREDIENTS: OCTINOXATE 7.5 g/100 g; OCTOCRYLENE 7 g/100 g; OCTISALATE 5 g/100 g; OXYBENZONE 5 g/100 g
INACTIVE INGREDIENTS: PETROLATUM; ISOPROPYL MYRISTATE; PARAFFIN; CANDELILLA WAX; LOW DENSITY POLYETHYLENE; CETYL ALCOHOL; LANOLIN; OLEYL ALCOHOL; OCTYLDODECANOL; PHENYL TRIMETHICONE; ALPHA-TOCOPHEROL ACETATE; ALOE VERA LEAF; SOYBEAN OIL; TITANIUM DIOXIDE; METHYLPARABEN; PROPYLPARABEN; SILICON DIOXIDE; SACCHARIN

time & again®
LIP BALM

Active ingredients

Octinoxate 7.5%, Octocrylene 7.0%, Octisalate 5.0%, Oxybenzone 5.0%

Purposes

Sunscreens

Use

- helps prevent sunburn

Warnings

- Stop use if skin rash occurs

Inactive ingredients

petrolatum, isopropyl myristate, paraffin, candelilla wax, synthetic beeswax, polyethylene, cetyl alcohol, lanolin, isopropyl lanolate, oleyl alcohol, octyldodecanol, phenyl trimethicone, flavor, tocopheryl acetate, aloe barbadensis leaf extract, glycine soja (soybean) oil, titanium dioxide, methylparaben, propylparaben, silica, saccharin, DEA-oleth-3-phosphate

Other information

You may report serious adverse reaction to this product to: Ganz U.S.A., LLC #043, 60 Industrial Parkway, Cheektowaga, New York, 14227-9903

MANUFACTURED FOR:
GANZ, Cheektowaga, N.Y. 14227-9903

PRINCIPAL DISPLAY PANEL - 4 g Carton

time & again®

LIP BALM

SPF 30
ALOE & VITAMIN E

UVA/UVB SUNSCREEN PROTECTION